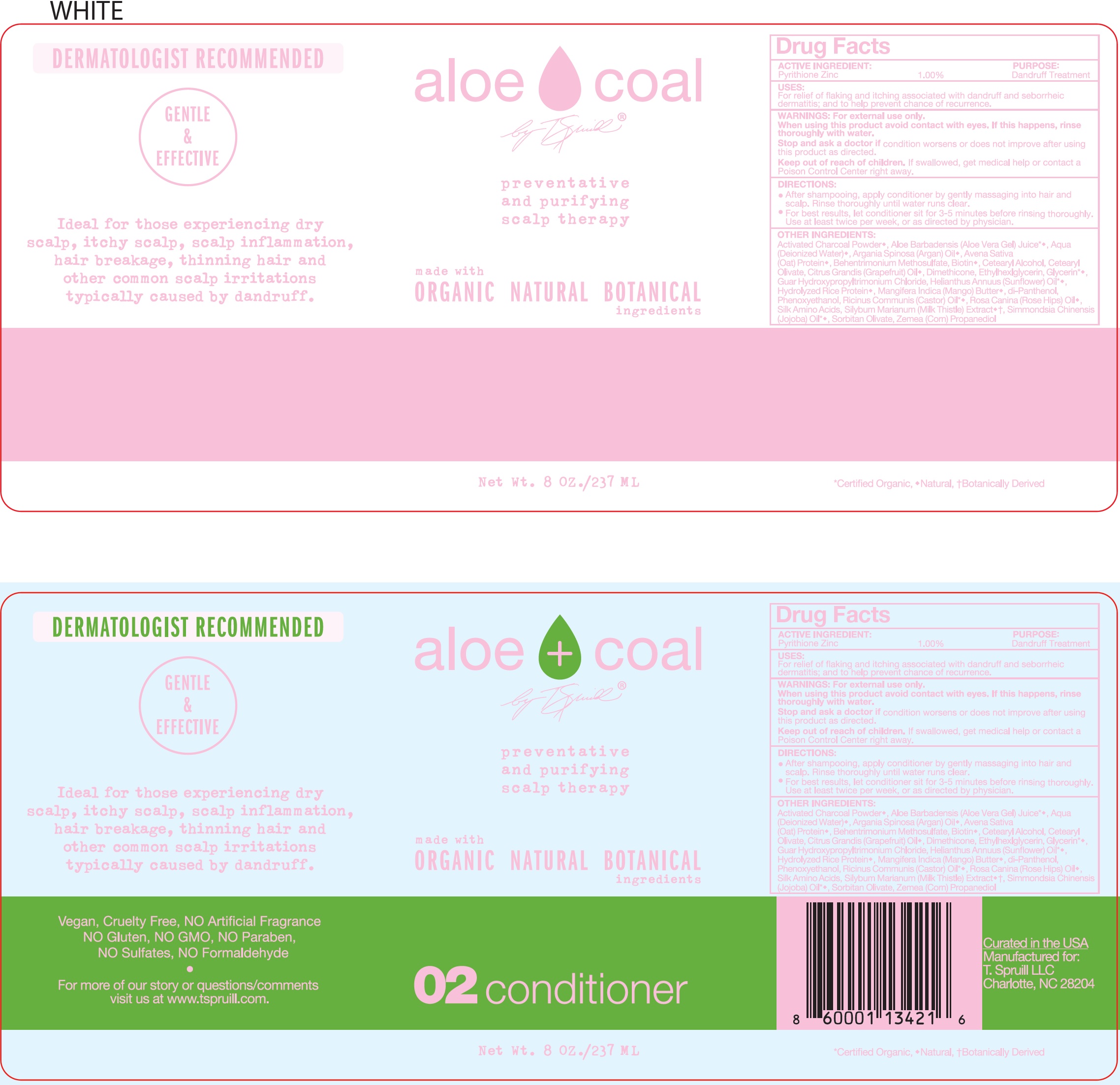 DRUG LABEL: Aloe Coal 02 Conditioner
NDC: 73324-090 | Form: LIQUID
Manufacturer: T. SPRUILL, LLC
Category: otc | Type: HUMAN OTC DRUG LABEL
Date: 20260119

ACTIVE INGREDIENTS: PYRITHIONE ZINC 10 mg/1 mL
INACTIVE INGREDIENTS: WATER; ARGAN OIL; OAT; BEHENTRIMONIUM METHOSULFATE; BIOTIN; CETOSTEARYL ALCOHOL; CETEARYL OLIVATE; GRAPEFRUIT; DIMETHICONE; ETHYLHEXYLGLYCERIN; GLYCERIN; GUAR HYDROXYPROPYLTRIMONIUM CHLORIDE (1.7 SUBSTITUENTS PER SACCHARIDE); HELIANTHUS ANNUUS FLOWERING TOP; MANGO; PHENOXYETHANOL; CASTOR OIL; ROSA CANINA FRUIT; AMINO ACIDS, SILK; MILK THISTLE; SORBITAN OLIVATE; CORN; PROPANEDIOL; ALOE VERA LEAF

Aloe + Coal 02 Conditioner

ACTIVE INGREDIENT:

Pyrithione Zinc 1.00%

PURPOSE

Dandruff Treatment

USES:

For relief of flaking and itching associated with dandruff and seborrheic dermatitis and to help prevent chance of recurrence.

WARNINGS

For external use only.

When using this product

avoid contact with eyes. If this happens, rinse thoroughly with water.

Stop and ask a doctor

if condition worsens or does not improve after using this product as directed.

Keep out of reach of children.

If swallowed, get medical help or contact a Poison Control Center right away.

DIRECTIONS:

After shampooing, apply conditioner by gently massaging into hair and scalp. Rinse thoroughly until water runs clear.

For best results, let conditioner sit for 3-5 minutes before rinsing thoroughly. Use a least twice per week, or as directed by physician.

OTHER INGREDIENTS:

Activated Charcoal Powder, Aloe Barbadensis (Aloe Vera Gel) Juice, Aqua (Deionized Water), Argania Spinosa (Argan) Oil, Avena Sativa (Oat) Protein, Behentrimonium Methosulfate, Biotin, Cetearyl Alcohol, Cetearyl Olivate, Citrus Grandis (Grapefruit) Oil, Dimethicone, Ethylhexylglycerin, Glycerin, Guar Hydroxypropyltrimonium Chloride, Helianthus Annuus (Sunflower) Oil, Hydrolyzed Rice Protein, Mangifera Indica (Mango) Butter, di-Panthenol, Phenoxyethanol, Ricinus Communis (Castor) Oil, Rosa Canina (Rose Hips) Oil, Silk Amino Acids, Silybum Marianum (Milk Thistle) Extract, Simmondsia Chinensis (Jojoba) Oil, Sorbitan Olivate, Zemea (Corn) Propanediol